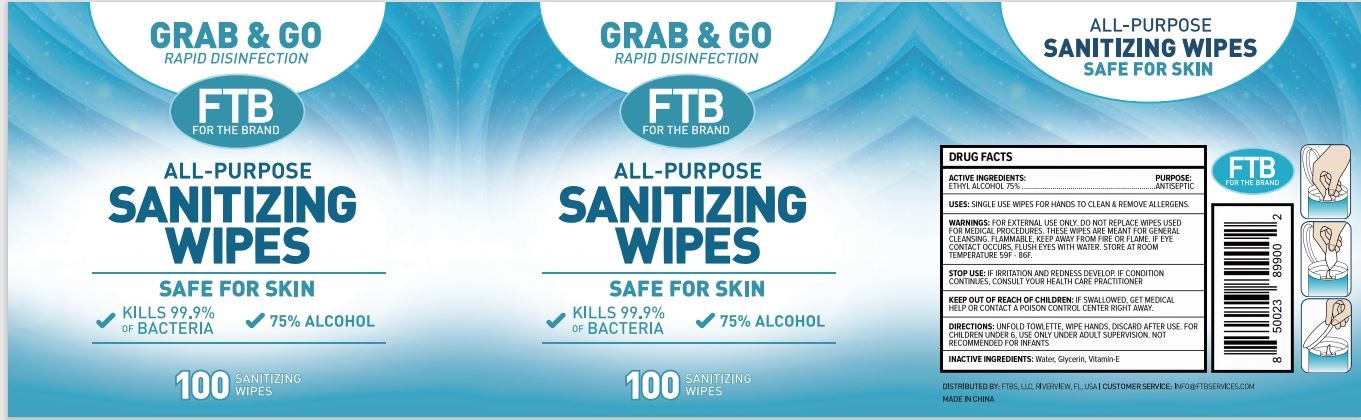 DRUG LABEL: ALL-PURPOSE SANITIZING WIPES
NDC: 79650-100 | Form: LIQUID
Manufacturer: Zhangzhou Zhongnan Nursing Products Co., Ltd.
Category: otc | Type: HUMAN OTC DRUG LABEL
Date: 20200929

ACTIVE INGREDIENTS: ALCOHOL 75 mL/100 mL
INACTIVE INGREDIENTS: GLYCERIN; ALPHA-TOCOPHEROL; WATER

ACTIVE INGREDIENT

Ethanol Alcohol 75%

PURPOSE

Antiseptic

INDICATIONS AND USAGE

SINGLE USE WIPES FOR HANDS TO CLEAN & REMOVE ALLERGENS.

WARNINGS

FOR EXTERNAL USE ONLY.DO NOT REPLACE USED FOR MEDICAL PROCEDURES. THESE WIPES ARE MEANT FOR GENERAL CLEANSING.FLAMMABLE. KEEP AWAY FROM FIRE OR FLAME. IF EYE CONTACT OCCURS, FLUSH EYES WITH WATER. STORE AT ROOM TEMPERATURE 59F-86F.

STOP USE: IF IRRITATION AND REDNESS DEVELOP. IF CONDITION CONTINUES, CONSULT YOUR HEALTH CARE PRACTITIONER.

KEEP OUT OF REACH OF CHILDREN: IF SWALLOWED, GET MEDICAL HELP OR CONTACT A POISON CONTROL CENTER RIGHT AWAY.

INACTIVE INGREDIENT

Water, Glycerin, Vitamin-E.

Directions

DIRECTIONS: UNFOLD TOWLETTE, WIPES HAND, DISCARD AFTER USE. FOR CHILDREN UNDER 6, USE ONLY UNDER ADULT SUPERVISION. NOT RECOMMENDED FOR INFANTS.

100pcs ALL-PURPOSE SANITIZING WIPES

100pcs Sanitizing Wipes, NDC: 79650-100-75